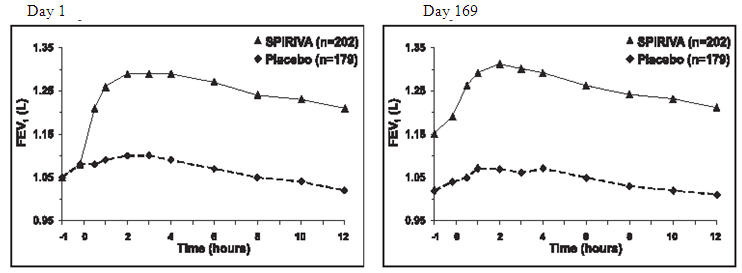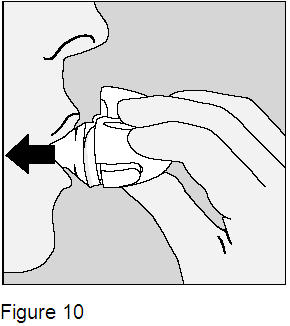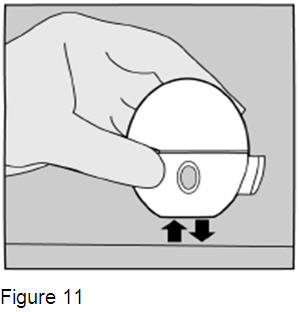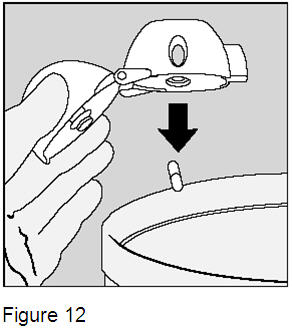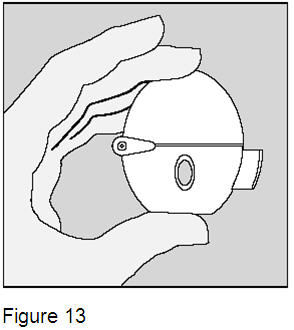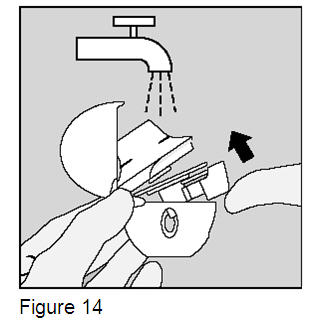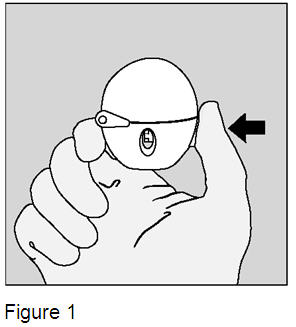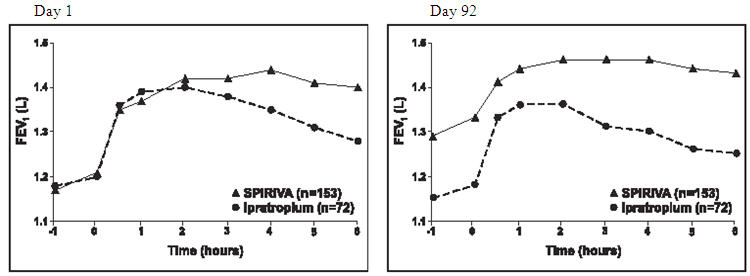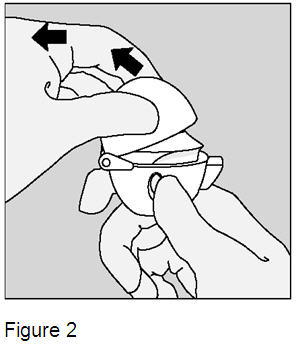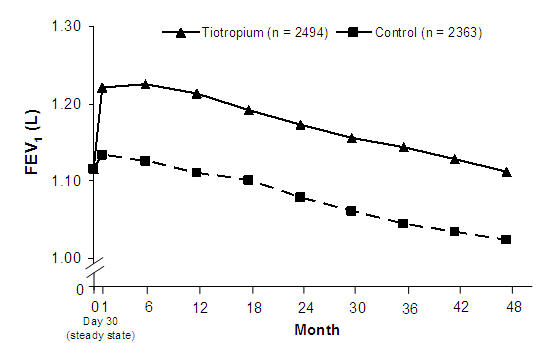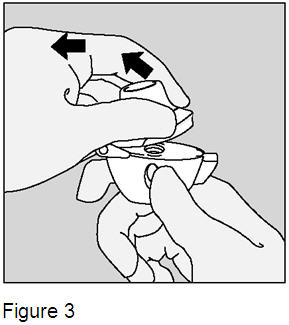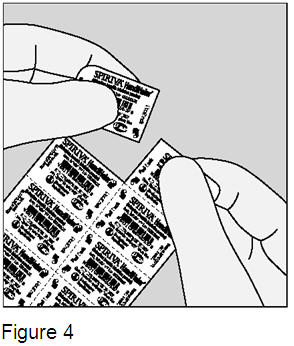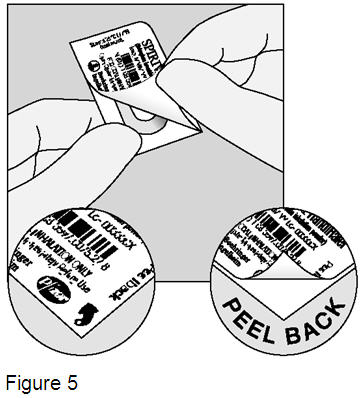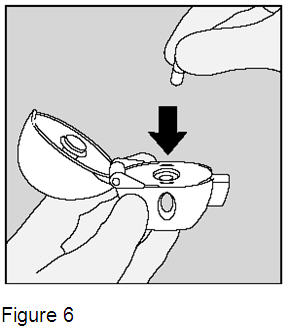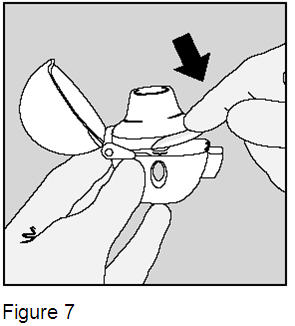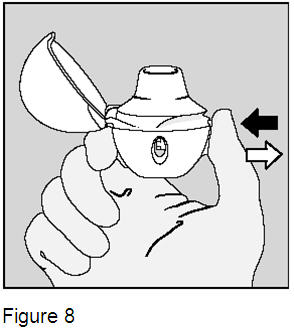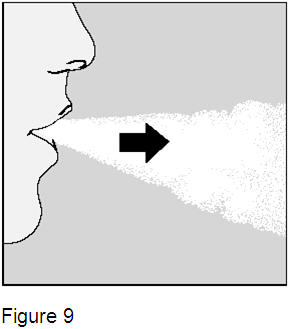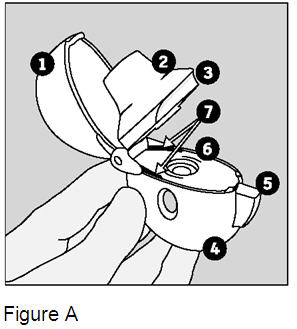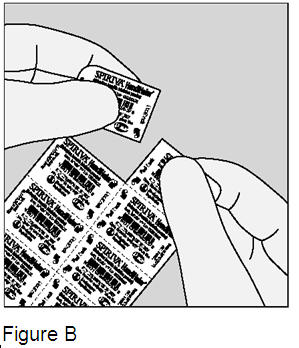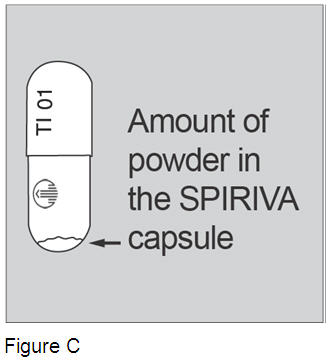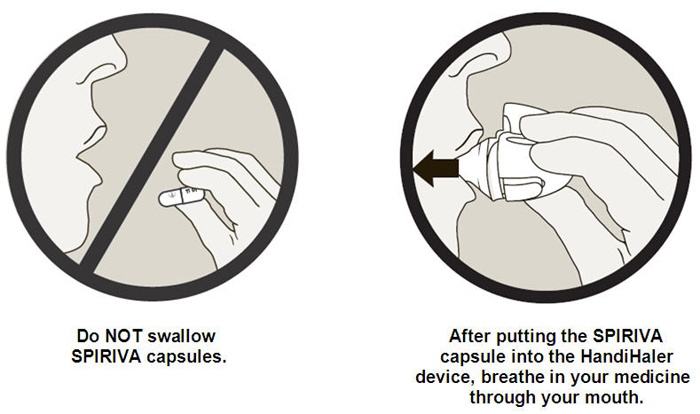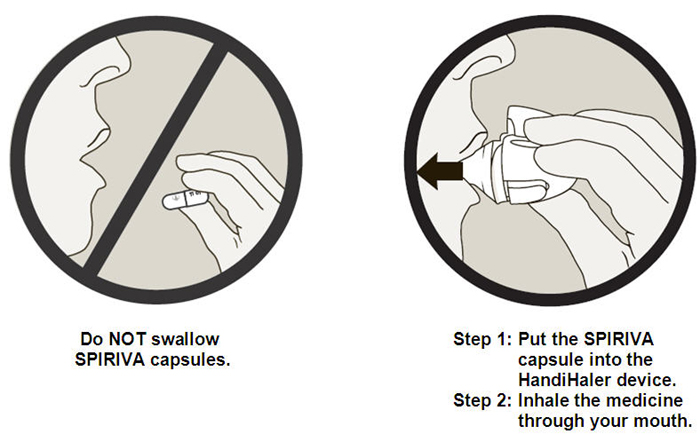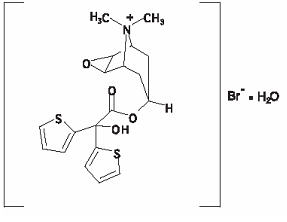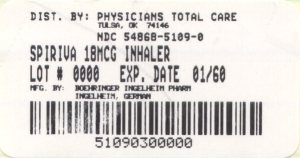 DRUG LABEL: Spiriva
NDC: 54868-5109 | Form: CAPSULE
Manufacturer: Physicians Total Care, Inc.
Category: prescription | Type: HUMAN PRESCRIPTION DRUG LABEL
Date: 20100318

ACTIVE INGREDIENTS: TIOTROPIUM BROMIDE MONOHYDRATE 18 ug/1 1
INACTIVE INGREDIENTS: LACTOSE MONOHYDRATE

HIGHLIGHTS OF PRESCRIBING INFORMATION

These highlights do not include all the information needed to use SPIRIVA HandiHaler safely and effectively. See full prescribing information for SPIRIVA HandiHaler.
SPIRIVA® HandiHaler® (tiotropium bromide inhalation powder)
Capsules for Respiratory Inhalation
DO NOT Swallow SPIRIVA Capsules
FOR ORAL INHALATION ONLY with the HandiHaler Device
Initial U.S. Approval: 2004

RECENT MAJOR CHANGES

Indications and Usage (1) | 12/2009
Dosage and Administration (2) | 12/2009
Contraindications (4) | 12/2009
Warnings and Precautions,
Immediate Hypersensitivity Reactions (5.2) | 12/2009
Worsening of Narrow-Angle Glaucoma (5.4) | 12/2009
Worsening of Urinary Retention (5.5) | 12/2009
Renal Impairment (5.6) | 12/2009

1 INDICATIONS AND USAGE

SPIRIVA HandiHaler is an anticholinergic indicated for the long-term, once-daily, maintenance treatment of bronchospasm associated with chronic obstructive pulmonary disease (COPD), and for reducing COPD exacerbations (1)

2 DOSAGE AND ADMINISTRATION

DO NOT swallow SPIRIVA capsules (2)

For Use with the HandiHaler Device ONLY (2)

For Oral Inhalation ONLY (2)

- Two inhalations of the powder contents of a single SPIRIVA capsule (18 mcg) once daily (2)

3 DOSAGE FORMS AND STRENGTHS

SPIRIVA capsules for oral inhalation: 18 mcg tiotropium powder, for use with HandiHaler device (3)

4 CONTRAINDICATIONS

- Hypersensitivity to ipratropium or tiotropium (4)

5 WARNINGS AND PRECAUTIONS

- Not for acute use: Not for use as a rescue medication (5.1)
- Immediate hypersensitivity reactions: Discontinue SPIRIVA HandiHaler at once and consider alternatives if immediate hypersensitivity reactions, including angioedema, occur. Use with caution in patients with severe hypersensitivity to milk proteins. (5.2)
- Paradoxical bronchospasm: Discontinue SPIRIVA HandiHaler and consider other treatments if paradoxical bronchospasm occurs (5.3)
- Worsening of narrow-angle glaucoma may occur. Use with caution in patients with narrow-angle glaucoma and instruct patients to consult a physician immediately if this occurs. (5.4)
- Worsening of urinary retention may occur. Use with caution in patients with prostatic hyperplasia or bladder-neck obstruction and instruct patients to consult a physician immediately if this occurs. (5.5)

6 ADVERSE REACTIONS

- The most common adverse reactions (>5% incidence in the 1-year placebo-controlled trials) were upper respiratory tract infection, dry mouth, sinusitis, pharyngitis, non-specific chest pain, urinary tract infection, dyspepsia, and rhinitis (6.1)

To report SUSPECTED ADVERSE REACTIONS, contact Boehringer Ingelheim Pharmaceuticals, Inc. at (800) 542-6257 or (800) 459-9906 TTY, or FDA at 1-800-FDA-1088 or www.fda.gov/medwatch.

7 DRUG INTERACTIONS

Not recommended for use with other anticholinergics since this has not been studied (7.2)

8 USE IN SPECIFIC POPULATIONS

Patients with moderate to severe renal impairment should be monitored closely for potential anticholinergic side effects (2, 8.6)

FULL PRESCRIBING INFORMATION

1 INDICATIONS AND USAGE

SPIRIVA HandiHaler (tiotropium bromide inhalation powder) is indicated for the long-term, once-daily, maintenance treatment of bronchospasm associated with chronic obstructive pulmonary disease (COPD), including chronic bronchitis and emphysema. SPIRIVA HandiHaler is indicated to reduce exacerbations in COPD patients.

2 DOSAGE AND ADMINISTRATION

DO NOT SWALLOW SPIRIVA CAPSULES
FOR USE WITH HANDIHALER DEVICE ONLY

FOR ORAL INHALATION ONLY

SPIRIVA capsules must not be swallowed as the intended effects on the lungs will not be obtained. The contents of the SPIRIVA capsules are only for oral inhalation and should only be used with the HandiHaler device [see Overdosage (10)].

The recommended dose of SPIRIVA HandiHaler is two inhalations of the powder contents of one SPIRIVA capsule, once-daily, with the HandiHaler device [see Patient Counseling Information (17.6)].

For administration of SPIRIVA HandiHaler, a SPIRIVA capsule is placed into the center chamber of the HandiHaler device. The SPIRIVA capsule is pierced by pressing and releasing the green piercing button on the side of the HandiHaler device. The tiotropium formulation is dispersed into the air stream when the patient inhales through the mouthpiece [see Patient Counseling Information (17.6)].

No dosage adjustment is required for geriatric, hepatically-impaired, or renally-impaired patients. However, patients with moderate to severe renal impairment given SPIRIVA HandiHaler should be monitored closely for anticholinergic effects [see Warnings and Precautions (5.6), Use in Specific Populations (8.5, 8.6, 8.7), and Clinical Pharmacology (12.3)].

3 DOSAGE FORMS AND STRENGTHS

SPIRIVA HandiHaler consists of SPIRIVA capsules and a HandiHaler device. SPIRIVA capsules contain 18 mcg dry powder formulation of tiotropium in a light green, hard gelatin capsule with TI 01 printed on one side and Boehringer Ingelheim company logo on the other side. Supplied with a HandiHaler device.

4 CONTRAINDICATIONS

SPIRIVA HandiHaler is contraindicated in patients with a hypersensitivity to ipratropium or tiotropium. In clinical trials and postmarketing experience with SPIRIVA HandiHaler, immediate hypersensitivity reactions, including angioedema (including swelling of the lips, tongue, or throat), itching, or rash have been reported.

5 WARNINGS AND PRECAUTIONS

5.1 Not for Acute Use

SPIRIVA HandiHaler is intended as a once-daily maintenance treatment for COPD and is not indicated for the initial treatment of acute episodes of bronchospasm (i.e., rescue therapy).

5.2 Immediate Hypersensitivity Reactions

Immediate hypersensitivity reactions, including angioedema (including swelling of the lips, tongue, or throat), itching, or rash may occur after administration of SPIRIVA HandiHaler. If such a reaction occurs, therapy with SPIRIVA HandiHaler should be stopped at once and alternative treatments should be considered. Given the similar structural formula of atropine to tiotropium, patients with a history of hypersensitivity reactions to atropine should be closely monitored for similar hypersensitivity reactions to SPIRIVA HandiHaler. In addition, SPIRIVA HandiHaler should be used with caution in patients with severe hypersensitivity to milk proteins.

5.3 Paradoxical Bronchospasm

Inhaled medicines, including SPIRIVA HandiHaler, may cause paradoxical bronchospasm. If this occurs, treatment with SPIRIVA HandiHaler should be stopped and other treatments considered.

5.4 Worsening of Narrow-Angle Glaucoma

SPIRIVA HandiHaler should be used with caution in patients with narrow-angle glaucoma. Prescribers and patients should be alert for signs and symptoms of acute narrow-angle glaucoma (e.g., eye pain or discomfort, blurred vision, visual halos or colored images in association with red eyes from conjunctival congestion and corneal edema). Instruct patients to consult a physician immediately should any of these signs or symptoms develop.

5.5 Worsening of Urinary Retention

SPIRIVA HandiHaler should be used with caution in patients with urinary retention. Prescribers and patients should be alert for signs and symptoms of prostatic hyperplasia or bladder-neck obstruction (e.g., difficulty passing urine, painful urination). Instruct patients to consult a physician immediately should any of these signs or symptoms develop.

5.6 Renal Impairment

As a predominantly renally excreted drug, patients with moderate to severe renal impairment (creatinine clearance of ≤50 mL/min) treated with SPIRIVA HandiHaler should be monitored closely for anticholinergic side effects [see Clinical Pharmacology (12.3)].

6 ADVERSE REACTIONS

The following adverse reactions are described, or described in greater detail, in other sections:

- Immediate hypersensitivity reactions [see Warnings and Precautions (5.2)]
- Paradoxical bronchospasm [see Warnings and Precautions (5.3)]
- Worsening of narrow-angle glaucoma [see Warnings and Precautions (5.4)]
- Worsening of urinary retention [see Warnings and Precautions (5.5)]

6.1 Clinical Trials Experience

Because clinical trials are conducted under widely varying conditions, adverse reaction rates observed in the clinical trials of a drug cannot be directly compared to rates in the clinical trials of another drug and may not reflect the rates observed in practice.

6-Month to 1-Year Trials

The data described below reflect exposure to SPIRIVA HandiHaler in 2663 patients. SPIRIVA HandiHaler was studied in two 1-year placebo-controlled trials, two 1-year active-controlled trials, and two 6-month placebo-controlled trials in patients with COPD. In these trials, 1308 patients were treated with SPIRIVA HandiHaler at the recommended dose of 18 mcg once a day. The population had an age ranging from 39 to 87 years with 65% to 85% males, 95% Caucasian, and had COPD with a mean pre-bronchodilator forced expiratory volume in one second (FEV1) percent predicted of 39% to 43%. Patients with narrow-angle glaucoma, or symptomatic prostatic hypertrophy or bladder outlet obstruction were excluded from these trials. An additional 6-month trial conducted in a Veteran's Affairs setting is not included in this safety database because only serious adverse events were collected.

The most commonly reported adverse drug reaction was dry mouth. Dry mouth was usually mild and often resolved during continued treatment. Other reactions reported in individual patients and consistent with possible anticholinergic effects included constipation, tachycardia, blurred vision, glaucoma (new onset or worsening), dysuria, and urinary retention.

Four multicenter, 1-year, placebo-controlled and active-controlled trials evaluated SPIRIVA HandiHaler in patients with COPD. Table 1 shows all adverse reactions that occurred with a frequency of ≥3% in the SPIRIVA HandiHaler group in the 1-year placebo-controlled trials where the rates in the SPIRIVA HandiHaler group exceeded placebo by ≥1%. The frequency of corresponding reactions in the ipratropium-controlled trials is included for comparison.

Table 1 Adverse Reactions (% Patients) in One-Year COPD Clinical Trials

Body System (Event) | Placebo-Controlled Trials |  | Ipratropium-Controlled Trials
 | SPIRIVA (n = 550) | Placebo (n = 371) | SPIRIVA (n = 356) | Ipratropium (n = 179)
Body as a Whole Chest Pain (non-specific) | 7 | 5 | 5 | 2
Edema, Dependent | 5 | 4 | 3 | 5
Gastrointestinal System Disorders Dry Mouth | 16 | 3 | 12 | 6
Dyspepsia | 6 | 5 | 1 | 1
Abdominal Pain | 5 | 3 | 6 | 6
Constipation | 4 | 2 | 1 | 1
Vomiting | 4 | 2 | 1 | 2
Musculoskeletal System Myalgia | 4 | 3 | 4 | 3
Resistance Mechanism Disorders Infection | 4 | 3 | 1 | 3
Moniliasis | 4 | 2 | 3 | 2
Respiratory System (Upper) Upper Respiratory Tract Infection | 41 | 37 | 43 | 35
Sinusitis | 11 | 9 | 3 | 2
Pharyngitis | 9 | 7 | 7 | 3
Rhinitis | 6 | 5 | 3 | 2
Epistaxis | 4 | 2 | 1 | 1
Skin and Appendage Disorders Rash | 4 | 2 | 2 | 2
Urinary System Urinary Tract Infection | 7 | 5 | 4 | 2

Arthritis, coughing, and influenza-like symptoms occurred at a rate of ≥3% in the SPIRIVA HandiHaler treatment group, but were <1% in excess of the placebo group.

Other reactions that occurred in the SPIRIVA HandiHaler group at a frequency of 1% to 3% in the placebo-controlled trials where the rates exceeded that in the placebo group include: Body as a Whole: allergic reaction, leg pain; Central and Peripheral Nervous System: dysphonia, paresthesia; Gastrointestinal System Disorders: gastrointestinal disorder not otherwise specified (NOS), gastroesophageal reflux, stomatitis (including ulcerative stomatitis); Metabolic and Nutritional Disorders: hypercholesterolemia, hyperglycemia; Musculoskeletal System Disorders: skeletal pain; Cardiac Events: angina pectoris (including aggravated angina pectoris); Psychiatric Disorder: depression; Infections: herpes zoster; Respiratory System Disorder (Upper): laryngitis; Vision Disorder: cataract. In addition, among the adverse reactions observed in the clinical trials with an incidence of <1% were atrial fibrillation, supraventricular tachycardia, angioedema, and urinary retention.

In the 1-year trials, the incidence of dry mouth, constipation, and urinary tract infection increased with age [see Use in Specific Populations (8.5)].

Two multicenter, 6-month, controlled studies evaluated SPIRIVA HandiHaler in patients with COPD. The adverse reactions and the incidence rates were similar to those seen in the 1-year controlled trials.

4-Year Trial
The data described below reflect exposure to SPIRIVA HandiHaler in 5992 COPD patients in a 4-year placebo-controlled trial. In this trial, 2986 patients were treated with SPIRIVA HandiHaler at the recommended dose of 18 mcg once a day. The population had an age range from 40 to 88 years, was 75% male, 90% Caucasian, and had COPD with a mean pre-bronchodilator FEV1 percent predicted of 40%. Patients with narrow-angle glaucoma, or symptomatic prostatic hypertrophy or bladder outlet obstruction were excluded from these trials. When the adverse reactions were analyzed with a frequency of ≥3% in the SPIRIVA HandiHaler group where the rates in the SPIRIVA HandiHaler group exceeded placebo by ≥1%, adverse reactions included (SPIRIVA HandiHaler, placebo): pharyngitis (12.5%, 10.8%), sinusitis (6.5%, 5.3%), headache (5.7%, 4.5%), constipation (5.1%, 3.7%), dry mouth (5.1%, 2.7%), depression (4.4%, 3.3%), insomnia (4.4%, 3.0%), and arthralgia (4.2%, 3.1%).

Additional Adverse Reactions
Other adverse reactions not previously listed that were reported more frequently in COPD patients treated with SPIRIVA HandiHaler than placebo include: dehydration, skin ulcer, stomatitis, gingivitis, oropharyngeal candidiasis, dry skin, skin infection, and joint swelling.

6.2 Postmarketing Experience

Adverse reactions have been identified during worldwide post-approval use of SPIRIVA HandiHaler. Because these reactions are reported voluntarily from a population of uncertain size, it is not always possible to reliably estimate their frequency or establish a causal relationship to drug exposure. These adverse reactions are: application site irritation (glossitis, mouth ulceration, and pharyngolaryngeal pain), dizziness, dysphagia, hoarseness, intestinal obstruction including ileus paralytic, intraocular pressure increased, oral candidiasis, palpitations, pruritus, tachycardia, throat irritation, and urticaria.

7 DRUG INTERACTIONS

7.1 Sympathomimetics, Methylxanthines, Steroids

SPIRIVA HandiHaler has been used concomitantly with short-acting and long-acting sympathomimetic (beta-agonists) bronchodilators, methylxanthines, and oral and inhaled steroids without increases in adverse drug reactions.

7.2 Anticholinergics

The co-administration of SPIRIVA HandiHaler with other anticholinergic-containing drugs (e.g., ipratropium) has not been studied and is therefore not recommended.

7.3 Cimetidine, Ranitidine

No clinically significant interaction occurred between tiotropium and cimetidine or ranitidine [see Clinical Pharmacology (12.3)].

8 USE IN SPECIFIC POPULATIONS

8.1 Pregnancy

Teratogenic Effects, Pregnancy Category C.
There are no adequate and well-controlled studies in pregnant women. SPIRIVA HandiHaler should be used during pregnancy only if the potential benefit justifies the potential risk to the fetus.

No evidence of structural alterations was observed in rats and rabbits at inhalation tiotropium doses of up to approximately 660 and 6 times the recommended human daily inhalation dose (RHDID) on a mg/m^2 basis, respectively. However, in rats, tiotropium caused fetal resorption, litter loss, decreases in the number of live pups at birth and the mean pup weights, and a delay in pup sexual maturation at inhalation tiotropium doses of approximately 35 times the RHDID on a mg/m^2 basis. In rabbits, tiotropium caused an increase in post-implantation loss at an inhalation dose of approximately 360 times the RHDID on a mg/m^2 basis. Such effects were not observed at inhalation doses of approximately 4 and 80 times the RHDID on a mg/m^2 basis, respectively. These dose multiples may be over-estimated due to difficulties in measuring deposited doses in animal inhalation studies.

8.2 Labor and Delivery

The safety and effectiveness of SPIRIVA HandiHaler has not been studied during labor and delivery.

8.3 Nursing Mothers

Clinical data from nursing women exposed to tiotropium are not available. Based on lactating rodent studies, tiotropium is excreted into breast milk. It is not known whether tiotropium is excreted in human milk, but because many drugs are excreted in human milk and given these findings in rats, caution should be exercised if SPIRIVA HandiHaler is administered to a nursing woman.

8.4 Pediatric Use

SPIRIVA HandiHaler is approved for use in the maintenance treatment of bronchospasm associated with COPD and for the reduction of COPD exacerbations. COPD does not normally occur in children. The safety and effectiveness of SPIRIVA HandiHaler in pediatric patients have not been established.

8.5 Geriatric Use

Of the total number of patients who received SPIRIVA HandiHaler in the 1-year clinical trials, 426 were <65 years, 375 were 65 to 74 years, and 105 were ≥75 years of age. Within each age subgroup, there were no differences between the proportion of patients with adverse events in the SPIRIVA HandiHaler and the comparator groups for most events. Dry mouth increased with age in the SPIRIVA HandiHaler group (differences from placebo were 9.0%, 17.1%, and 16.2% in the aforementioned age subgroups). A higher frequency of constipation and urinary tract infections with increasing age was observed in the SPIRIVA HandiHaler group in the placebo-controlled studies. The differences from placebo for constipation were 0%, 1.8%, and 7.8% for each of the age groups. The differences from placebo for urinary tract infections were –0.6%, 4.6%, and 4.5%. No overall differences in effectiveness were observed among these groups. Based on available data, no adjustment of SPIRIVA HandiHaler dosage in geriatric patients is warranted [see Clinical Pharmacology (12.3)].

8.6 Renal Impairment

Patients with moderate to severe renal impairment (creatinine clearance of ≤50 mL/min) treated with SPIRIVA HandiHaler should be monitored closely for anticholinergic side effects [see Dosage and Administration (2), Warnings and Precautions (5.4), and Clinical Pharmacology (12.3)].

8.7 Hepatic Impairment

The effects of hepatic impairment on the pharmacokinetics of tiotropium were not studied.

10 OVERDOSAGE

High doses of tiotropium may lead to anticholinergic signs and symptoms. However, there were no systemic anticholinergic adverse effects following a single inhaled dose of up to 282 mcg tiotropium in 6 healthy volunteers. In a study of 12 healthy volunteers, bilateral conjunctivitis and dry mouth were seen following repeated once-daily inhalation of 141 mcg of tiotropium.

Accidental Ingestion
Acute intoxication by inadvertent oral ingestion of SPIRIVA capsules is unlikely since it is not well-absorbed systemically.

A case of overdose has been reported from postmarketing experience. A female patient was reported to have inhaled 30 capsules over a 2.5 day period, and developed altered mental status, tremors, abdominal pain, and severe constipation. The patient was hospitalized, SPIRIVA HandiHaler was discontinued, and the constipation was treated with an enema. The patient recovered and was discharged on the same day.

No mortality was observed at inhalation tiotropium doses up to 32.4 mg/kg in mice, 267.7 mg/kg in rats, and 0.6 mg/kg in dogs. These doses correspond to 7300, 120,000, and 850 times the recommended human daily inhalation dose on a mg/m^2 basis, respectively. These dose multiples may be over-estimated due to difficulties in measuring deposited doses in animal inhalation studies.

11 DESCRIPTION

SPIRIVA HandiHaler consists of a capsule dosage form containing a dry powder formulation of tiotropium intended for oral inhalation only with the HandiHaler device.

Each light green, hard gelatin SPIRIVA capsule contains 18 mcg tiotropium (equivalent to 22.5 mcg tiotropium bromide monohydrate) blended with lactose monohydrate (which may contain milk proteins) as the carrier.

The dry powder formulation within the SPIRIVA capsule is intended for oral inhalation only.

The active component of SPIRIVA HandiHaler is tiotropium. The drug substance, tiotropium bromide monohydrate, is an anticholinergic with specificity for muscarinic receptors. It is chemically described as (1α, 2ß, 4ß, 5α, 7ß)-7-[(Hydroxydi-2-thienylacetyl)oxy]-9,9-dimethyl-3-oxa-9-azoniatricyclo[3.3.1.0^2,4]nonane bromide monohydrate. It is a synthetic, non-chiral, quaternary ammonium compound. Tiotropium bromide is a white or yellowish white powder. It is sparingly soluble in water and soluble in methanol.

The structural formula is:

Tiotropium bromide (monohydrate) has a molecular mass of 490.4 and a molecular formula of C19H22NO4S2Br • H2O.

The HandiHaler device is an inhalation device used to inhale the dry powder contained in the SPIRIVA capsule. The dry powder is delivered from the HandiHaler device at flow rates as low as 20 L/min. Under standardized in vitro testing, the HandiHaler device delivers a mean of 10.4 mcg tiotropium when tested at a flow rate of 39 L/min for 3.1 seconds (2 L total). In a study of 26 adult patients with COPD and severely compromised lung function [mean FEV1 1.02 L (range 0.45 to 2.24 L); 37.6% of predicted (range 16% to 65%)], the median peak inspiratory flow (PIF) through the HandiHaler device was 30.0 L/min (range 20.4 to 45.6 L/min). The amount of drug delivered to the lungs will vary depending on patient factors such as inspiratory flow and peak inspiratory flow through the HandiHaler device, which may vary from patient to patient, and may vary with the exposure time of the SPIRIVA capsule outside the blister pack.

12 CLINICAL PHARMACOLOGY

12.1 Mechanism of Action

Tiotropium is a long-acting, antimuscarinic agent, which is often referred to as an anticholinergic. It has similar affinity to the subtypes of muscarinic receptors, M1 to M5. In the airways, it exhibits pharmacological effects through inhibition of M3-receptors at the smooth muscle leading to bronchodilation. The competitive and reversible nature of antagonism was shown with human and animal origin receptors and isolated organ preparations. In preclinical in vitro as well as in vivo studies, prevention of methacholine-induced bronchoconstriction effects was dose-dependent and lasted longer than 24 hours. The bronchodilation following inhalation of tiotropium is predominantly a site-specific effect.

12.2 Pharmacodynamics

Cardiovascular Effects
In a multicenter, randomized, double-blind trial that enrolled 198 patients with COPD, the number of subjects with changes from baseline-corrected QT interval of 30 to 60 msec was higher in the SPIRIVA HandiHaler group as compared with placebo. This difference was apparent using both the Bazett (QTcB) [20 (20%) patients vs 12 (12%) patients] and Fredericia (QTcF) [16 (16%) patients vs 1 (1%) patient] corrections of QT for heart rate. No patients in either group had either QTcB or QTcF of >500 msec. Other clinical studies with SPIRIVA HandiHaler did not detect an effect of the drug on QTc intervals.

The effect of SPIRIVA HandiHaler on QT interval was also evaluated in a randomized, placebo- and positive-controlled crossover study in 53 healthy volunteers. Subjects received SPIRIVA HandiHaler 18 mcg, 54 mcg (3 times the recommended dose), or placebo for 12 days. ECG assessments were performed at baseline and throughout the dosing interval following the first and last dose of study medication. Relative to placebo, the maximum mean change from baseline in study-specific QTc interval was 3.2 msec and 0.8 msec for SPIRIVA HandiHaler 18 mcg and 54 mcg, respectively. No subject showed a new onset of QTc >500 msec or QTc changes from baseline of ≥60 msec.

12.3 Pharmacokinetics

Tiotropium is administered by dry powder inhalation. In common with other inhaled drugs, the majority of the delivered dose is deposited in the gastrointestinal tract and, to a lesser extent, in the lung, the intended organ. Many of the pharmacokinetic data described below were obtained with higher doses than recommended for therapy.

Absorption
Following dry powder inhalation by young healthy volunteers, the absolute bioavailability of 19.5% suggests that the fraction reaching the lung is highly bioavailable. It is expected from the chemical structure of the compound (quaternary ammonium compound) that tiotropium is poorly absorbed from the gastrointestinal tract. The effect of food on tiotropium's bioavailability has not been studied. Oral solutions of tiotropium have an absolute bioavailability of 2% to 3%. Maximum tiotropium plasma concentrations were observed 5 minutes after inhalation.

Distribution
Tiotropium shows a volume of distribution of 32 L/kg indicating that the drug binds extensively to tissues. The human plasma protein binding for tiotropium is 72%. At steady state, peak tiotropium plasma levels in COPD patients were 17 to 19 pg/mL when measured 5 minutes after dry powder inhalation of an 18 mcg dose and decreased in a multi-compartmental manner. Steady-state trough plasma concentrations were 3 to 4 pg/mL. Local concentrations in the lung are not known, but the mode of administration suggests substantially higher concentrations in the lung. Studies in rats have shown that tiotropium does not readily penetrate the blood-brain barrier.

Metabolism
The extent of metabolism appears to be small. This is evident from a urinary excretion of 74% of unchanged substance after an intravenous dose to young healthy volunteers. Tiotropium, an ester, is nonenzymatically cleaved to the alcohol N-methylscopine and dithienylglycolic acid, neither of which bind to muscarinic receptors.

In vitro experiments with human liver microsomes and human hepatocytes suggest that a fraction of the administered dose (74% of an intravenous dose is excreted unchanged in the urine, leaving 25% for metabolism) is metabolized by cytochrome P450-dependent oxidation and subsequent glutathione conjugation to a variety of Phase II metabolites. This enzymatic pathway can be inhibited by CYP450 2D6 and 3A4 inhibitors, such as quinidine, ketoconazole, and gestodene. Thus, CYP450 2D6 and 3A4 are involved in the metabolic pathway that is responsible for the elimination of a small part of the administered dose. In vitro studies using human liver microsomes showed that tiotropium in supra-therapeutic concentrations did not inhibit CYP450 1A1, 1A2, 2B6, 2C9, 2C19, 2D6, 2E1, or 3A4.

Elimination
The terminal elimination half-life of tiotropium was between 5 and 6 days following inhalation. Total clearance was 880 mL/min after an intravenous dose in young healthy volunteers with an inter-individual variability of 22%. Intravenously administered tiotropium was mainly excreted unchanged in urine (74%). After dry powder inhalation, urinary excretion was 14% of the dose, the remainder being mainly non-absorbed drug in the gut which was eliminated via the feces. The renal clearance of tiotropium exceeds the creatinine clearance, indicating active secretion into the urine. After chronic once-daily inhalation by COPD patients, pharmacokinetic steady state was reached after 2 to 3 weeks with no accumulation thereafter.

Drug Interactions
An interaction study with tiotropium (14.4 mcg intravenous infusion over 15 minutes) and cimetidine 400 mg three times daily or ranitidine 300 mg once daily was conducted. Concomitant administration of cimetidine with tiotropium resulted in a 20% increase in the AUC0-4h, a 28% decrease in the renal clearance of tiotropium and no significant change in the Cmax and amount excreted in urine over 96 hours. Co-administration of tiotropium with ranitidine did not affect the pharmacokinetics of tiotropium.

Specific Populations
Geriatric Patients
As expected for drugs predominantly excreted renally, advanced age was associated with a decrease of tiotropium renal clearance (326 mL/min in COPD patients <58 years to 163 mL/min in COPD patients >70 years), which may be explained by decreased renal function. Tiotropium excretion in urine after inhalation decreased from 14% (young healthy volunteers) to about 7% (COPD patients). Plasma concentrations were numerically increased with advancing age within COPD patients (43% increase in AUC0-4 after dry powder inhalation), which was not significant when considered in relation to inter- and intra-individual variability [see Dosage and Administration (2) and Use in Specific Populations (8.5)].

Renal Impairment
Since tiotropium is predominantly renally excreted, renal impairment was associated with increased plasma drug concentrations and reduced drug clearance after both intravenous infusion and dry powder inhalation. Mild renal impairment (creatinine clearance of 50 to 80 mL/min), which is often seen in elderly patients, increased tiotropium plasma concentrations (39% increase in AUC0-4 after intravenous infusion). In COPD patients with moderate to severe renal impairment (creatinine clearance of <50 mL/min), the intravenous administration of tiotropium resulted in doubling of the plasma concentrations (82% increase in AUC0-4), which was confirmed by plasma concentrations after dry powder inhalation. Patients with moderate to severe renal impairment (creatinine clearance of ≤50 mL/min) treated with SPIRIVA HandiHaler should be monitored closely for anticholinergic side effects [see Dosage and Administration (2),Warnings and Precautions (5.4), and Use in Specific Populations (8.6)].

Hepatic Impairment
The effects of hepatic impairment on the pharmacokinetics of tiotropium were not studied.

13 NONCLINICAL TOXICOLOGY

13.1 Carcinogenesis, Mutagenesis, Impairment of Fertility

No evidence of tumorigenicity was observed in a 104-week inhalation study in rats at tiotropium doses up to 0.059 mg/kg/day, in an 83-week inhalation study in female mice at doses up to 0.145 mg/kg/day, and in a 101-week inhalation study in male mice at doses up to 0.002 mg/kg/day. These doses correspond to approximately 25, 35, and 0.5 times the recommended human daily inhalation dose (RHDID) on a mg/m^2 basis, respectively. These dose multiples may be over-estimated due to difficulties in measuring deposited doses in animal inhalation studies.

Tiotropium bromide demonstrated no evidence of mutagenicity or clastogenicity in the following assays: the bacterial gene mutation assay, the V79 Chinese hamster cell mutagenesis assay, the chromosomal aberration assays in human lymphocytes in vitro and mouse micronucleus formation in vivo, and the unscheduled DNA synthesis in primary rat hepatocytes in vitro assay.

In rats, decreases in the number of corpora lutea and the percentage of implants were noted at inhalation tiotropium doses of 0.078 mg/kg/day or greater (approximately 35 times the RHDID on a mg/m^2 basis). No such effects were observed at 0.009 mg/kg/day (approximately 4 times than the RHDID on a mg/m^2 basis). The fertility index, however, was not affected at inhalation doses up to 1.689 mg/kg/day (approximately 760 times the RHDID on a mg/m^2 basis). These dose multiples may be over-estimated due to difficulties in measuring deposited doses in animal inhalation studies.

13.2 Animal Toxicology and Pharmacology

Reproductive Toxicology Studies
No evidence of fetal structural alteration was observed in rats and rabbits at inhalation tiotropium doses of up to 1.471 and 0.007 mg/kg/day, respectively. These doses correspond to approximately 660 and 6 times the RHDID on a mg/m^2 basis, respectively. However, in rats, fetal resorption, litter loss, decreases in the number of live pups at birth and the mean pup weights, and a delay in pup sexual maturation were observed at inhalation tiotropium doses of ≥0.078 mg/kg (approximately 35 times the RHDID on a mg/m^2 basis). In rabbits, an increase in post-implantation loss was observed at an inhalation dose of 0.4 mg/kg/day (approximately 360 times the RHDID on a mg/m^2 basis). Such effects were not observed at inhalation doses of 0.009 and up to 0.088 mg/kg/day in rats and rabbits, respectively. These doses correspond to approximately 4 and 80 times the RHDID on a mg/m^2 basis, respectively. These dose multiples may be over-estimated due to difficulties in measuring deposited doses in animal inhalation studies.

14 CLINICAL STUDIES

The SPIRIVA HandiHaler (tiotropium bromide inhalation powder) clinical development program consisted of six Phase 3 studies in 2663 patients with COPD (1308 receiving SPIRIVA HandiHaler): two 1-year, placebo‑controlled studies, two 6-month, placebo-controlled studies and two 1-year, ipratropium-controlled studies. These studies enrolled patients who had a clinical diagnosis of COPD, were 40 years of age or older, had a history of smoking greater than 10 pack-years, had a forced expiratory volume in one second (FEV1) less than or equal to 60% or 65% of predicted, and a ratio of FEV1/FVC of less than or equal to 0.7.

In these studies, SPIRIVA HandiHaler, administered once-daily in the morning, provided improvement in lung function (FEV1), with peak effect occurring within 3 hours following the first dose.

Two additional trials evaluated exacerbations: a 6-month, randomized, double-blind, placebo-controlled, multicenter clinical trial of 1829 COPD patients in a US Veterans Affairs setting and a 4-year, randomized, double-blind, placebo-controlled, multicenter, clinical trial of 5992 COPD patients. Long-term effects on lung function and other outcomes were also evaluated in the 4-year multicenter trial.

6-Month to 1-Year Effects on Lung Function
In the 1-year, placebo-controlled trials, the mean improvement in FEV1 at 30 minutes was 0.13 liters (13%) with a peak improvement of 0.24 liters (24%) relative to baseline after the first dose (Day 1). Further improvements in FEV1 and forced vital capacity (FVC) were observed with pharmacodynamic steady state reached by Day 8 with once-daily treatment. The mean peak improvement in FEV1, relative to baseline, was 0.28 to 0.31 liters (28% to 31%), after 1 week (Day 8) of once-daily treatment. Improvement of lung function was maintained for 24 hours after a single dose and consistently maintained over the 1-year treatment period with no evidence of tolerance.

In the two 6-month, placebo-controlled trials, serial spirometric evaluations were performed throughout daytime hours in Trial A (12 hours) and limited to 3 hours in Trial B. The serial FEV1 values over 12 hours (Trial A) are displayed in Figure 1. These trials further support the improvement in pulmonary function (FEV1) with SPIRIVA HandiHaler, which persisted over the spirometric observational period. Effectiveness was maintained for 24 hours after administration over the 6-month treatment period.

Figure 1 Mean FEV1 Over Time (prior to and after administration of study drug) on Days 1 and 169 for Trial A (a Six-Month Placebo-Controlled Study)*

*Means adjusted for center, treatment, and baseline effect. On Day 169, a total of 183 and 149 patients in the SPIRIVA HandiHaler and placebo groups, respectively, completed the trial. The data for the remaining patients were imputed using the last observation or least favorable observation carried forward.

Results of each of the 1-year ipratropium-controlled trials were similar to the results of the 1-year placebo-controlled trials. The results of one of these trials are shown in Figure 2.

Figure 2 Mean FEV1 Over Time (0 to 6 hours post-dose) on Days 1 and 92, Respectively for One of the Two Ipratropium-Controlled Studies*

*Means adjusted for center, treatment, and baseline effect. On Day 92 (primary endpoint), a total of 151 and 69 patients in the SPIRIVA HandiHaler and ipratropium groups, respectively, completed through 3 months of observation. The data for the remaining patients were imputed using the last observation or least favorable observation carried forward.

A randomized, placebo-controlled clinical study in 105 patients with COPD demonstrated that bronchodilation was maintained throughout the 24-hour dosing interval in comparison to placebo, regardless of whether SPIRIVA HandiHaler was administered in the morning or in the evening.

Throughout each week of the one-year treatment period in the two placebo-controlled trials, patients taking SPIRIVA HandiHaler had a reduced requirement for the use of rescue short-acting beta2-agonists. Reduction in the use of rescue short-acting beta2-agonists, as compared to placebo, was demonstrated in one of the two 6-month studies.

4-Year Effects on Lung Function
A 4-year, randomized, double-blind, placebo-controlled, multicenter clinical trial involving 5992 COPD patients was conducted to evaluate the long-term effects of SPIRIVA HandiHaler on disease progression (rate of decline in FEV1). Patients were permitted to use all respiratory medications (including short-acting and long-acting beta-agonists, inhaled and systemic steroids, and theophyllines) other than inhaled anticholinergics. The patients were 40 to 88 years of age, 75% male, and 90% Caucasian with a diagnosis of COPD and a mean pre-bronchodilator FEV1 of 39% predicted (range = 9% to 76%) at study entry. There was no difference between the groups in either of the co-primary efficacy endpoints, yearly rate of decline in pre- and post-bronchodilator FEV1, as demonstrated by similar slopes of FEV1 decline over time (Figure 3).

SPIRIVA HandiHaler maintained improvements in trough (pre-dose) FEV1 (adjusted means over time: 87 to 103 mL) throughout the 4 years of the study (Figure 3).

Figure 3 Trough (pre-dose) FEV1 Mean Values at Each Time Point

Repeated measure ANOVA was used to estimate means. Means are adjusted for baseline measurements. Baseline trough FEV1 (observed mean) = 1.12. Patients with ≥3 acceptable pulmonary function tests after Day 30 and non-missing baseline value were included in the analysis.

Exacerbations
The effect of SPIRIVA HandiHaler on COPD exacerbations was evaluated in two clinical trials: a 4-year clinical trial described above and a 6-month clinical trial of 1829 COPD patients in a Veterans Affairs setting. In the 6-month trial, COPD exacerbations were defined as a complex of respiratory symptoms (increase or new onset) of more than one of the following: cough, sputum, wheezing, dyspnea, or chest tightness with a duration of at least 3 days requiring treatment with antibiotics, systemic steroids, or hospitalization. The population had an age ranging from 40 to 90 years with 99% males, 91% Caucasian, and had COPD with a mean pre-bronchodilator FEV1 percent predicted of 36% (range = 8% to 93%). Patients were permitted to use respiratory medications (including short-acting and long-acting beta-agonists, inhaled and systemic steroids, and theophyllines) other than inhaled anticholinergics. In the 6-month trial, the co-primary endpoints were the proportion of patients with COPD exacerbation and the proportion of patients with hospitalization due to COPD exacerbation. SPIRIVA HandiHaler significantly reduced the proportion of COPD patients who experienced exacerbations compared to placebo (27.9% vs 32.3%, respectively; Odds Ratio (OR) (tiotropium/placebo) = 0.81; 95% CI = 0.66, 0.99; p = 0.037). The proportion of patients with hospitalization due to COPD exacerbations in patients who used SPIRIVA HandiHaler compared to placebo was 7.0% vs 9.5%, respectively; OR = 0.72; 95% CI = 0.51, 1.01; p = 0.056.

Exacerbations were evaluated as a secondary outcome in the 4-year multicenter trial. In this trial, COPD exacerbations were defined as an increase or new onset of more than one of the following respiratory symptoms (cough, sputum, sputum purulence, wheezing, dyspnea) with a duration of three or more days requiring treatment with antibiotics and/or systemic (oral, intramuscular, or intravenous) steroids. SPIRIVA HandiHaler significantly reduced the risk of an exacerbation by 14% (Hazard Ratio (HR) = 0.86; 95% CI = 0.81, 0.91; p<0.001) and reduced the risk of exacerbation-related hospitalization by 14% (HR = 0.86; 95% CI = 0.78, 0.95; p<0.002) compared to placebo. The median time to first exacerbation was delayed from 12.5 months (95% CI = 11.5, 13.8) in the placebo group to 16.7 months (95% CI = 14.9, 17.9) in the SPIRIVA HandiHaler group.

16 HOW SUPPLIED/STORAGE AND HANDLING

SPIRIVA HandiHaler consists of SPIRIVA capsules and the HandiHaler device. SPIRIVA capsules contain 18 mcg of tiotropium and are light green, with the Boehringer Ingelheim company logo on the SPIRIVA capsule cap and TI 01 on the SPIRIVA capsule body, or vice versa.

The HandiHaler device is gray colored with a green piercing button. It is imprinted with SPIRIVA HandiHaler (tiotropium bromide inhalation powder), the Boehringer Ingelheim company logo, and the Pfizer company logo. It is also imprinted to indicate that SPIRIVA capsules should not be stored in the HandiHaler device and that the HandiHaler device is only to be used with SPIRIVA capsules.

SPIRIVA capsules are packaged in an aluminum/aluminum blister card and joined along a perforated-cut line. SPIRIVA capsules should always be stored in the blister and only removed immediately before use. The drug should be used immediately after the packaging over an individual SPIRIVA capsule is opened.

The following packages are available:

- carton containing 6 SPIRIVA capsules (5 unit-dose blister cards) and 1 HandiHaler inhalation device (NDC 54868-5109-0)
- carton containing 90 SPIRIVA capsules (9 unit-dose blister cards) and 1 HandiHaler inhalation device (NDC 54868-5109-1)

Storage
Store at 25°C (77°F); excursions permitted to 15°–30°C (59°–86°F) [see USP Controlled Room Temperature].

The SPIRIVA capsules should not be exposed to extreme temperature or moisture. Do not store SPIRIVA capsules in the HandiHaler device.

17 PATIENT COUNSELING INFORMATION

See FDA-approved Patient Labeling (17.6)

17.1 Instructions for Administering SPIRIVA HandiHaler

It is important for patients to understand how to correctly administer SPIRIVA capsules using the HandiHaler device [see Patient Counseling Information (17.6)]. Patients should be instructed that SPIRIVA capsules should only be administered via the HandiHaler device and the HandiHaler device should not be used for administering other medications. The contents of SPIRIVA capsules are for oral inhalation only and must not be swallowed.

SPIRIVA capsules should always be stored in sealed blisters. Only one SPIRIVA capsule should be removed immediately before use or its effectiveness may be reduced. Additional SPIRIVA capsules that are exposed to air (i.e., not intended for immediate use) should be discarded.

17.2 Paradoxical Bronchospasm

Patients should be informed that SPIRIVA HandiHaler can produce paradoxical bronchospasm. If paradoxical bronchospasm occurs, patients should discontinue SPIRIVA HandiHaler.

17.3 Urinary Retention

Difficulty passing urine and dysuria may be symptoms of new or worsening prostatic hyperplasia or bladder outlet obstruction. Patients should be instructed to consult a physician immediately should any of these signs or symptoms develop.

17.4 Visual Effects

Eye pain or discomfort, blurred vision, visual halos or colored images in association with red eyes from conjunctival congestion and corneal edema may be signs of acute narrow-angle glaucoma. Patients should be told to consult a physician immediately should any of these signs and symptoms develop. Miotic eye drops alone are not considered to be effective treatment.

Patients should be told that care must be taken not to allow the powder to enter into the eyes as this may cause blurring of vision and pupil dilation.

17.5 Acute Exacerbation

Patients should understand that SPIRIVA HandiHaler is a once-daily maintenance bronchodilator and should not be used for immediate relief of breathing problems (i.e., as a rescue medication).

17.6 FDA-approved Patient Labeling

Patient Information and Patient’s Instructions for Use are supplied as tear-off leaflets following the full prescribing information and should be dispensed with each new prescription and refill.

Distributed by:
Boehringer Ingelheim Pharmaceuticals, Inc.
Ridgefield, CT 06877 USA

Marketed by:
Boehringer Ingelheim Pharmaceuticals, Inc.
Ridgefield, CT 06877 USA
and
Pfizer Inc
New York, NY 10017 USA

Licensed from:
Boehringer Ingelheim International GmbH

Address medical inquiries to: (800) 542-6257 or (800) 459-9906 TTY.

SPIRIVA® and HandiHaler® are registered trademarks and are used under license from Boehringer Ingelheim International GmbH.

©Copyright 2009 Boehringer Ingelheim International GmbH
ALL RIGHTS RESERVED

SPIRIVA® (tiotropium bromide inhalation powder) is covered by U.S. Patent Nos. RE38,912, RE39,820, 5,478,578, 6,777,423, 6,908,928, 7,070,800, and 7,309,707 with other patents pending. The HandiHaler® inhalation device is covered by U.S. Design Patent No. D355,029 with other patents pending.

Rev: December 2009

IT1600WL1609
10004551/07
65626-08

Relabeling of "Additional Barcode" by:
Physicians Total Care, Inc.
Tulsa, OK 74146

Patient Information

SPIRIVA® (speh REE vah) HandiHaler®
(tiotropium bromide inhalation powder)

Important Information: Do not swallow SPIRIVA capsules. SPIRIVA capsules should only be used with the HandiHaler device. SPIRIVA HandiHaler should only be inhaled by mouth (oral inhalation).

Read the information that comes with your SPIRIVA HandiHaler before you start using it and each time you refill your prescription. There may be new information. This leaflet does not take the place of talking with your doctor about your medical condition or your treatment.

What is SPIRIVA HandiHaler?
SPIRIVA HandiHaler is a prescription medicine that you use one time every day (a maintenance medicine) to control symptoms of chronic obstructive pulmonary disease (COPD). SPIRIVA HandiHaler helps make your lungs work better for 24 hours. SPIRIVA HandiHaler relaxes your airways and helps keep them open. You may start to feel like it is easier to breathe on the first day, but it may take longer for you to feel the full effects of the medicine. SPIRIVA HandiHaler works best and may help make it easier to breathe when you use it every day.

SPIRIVA HandiHaler also reduces the likelihood of flare-ups and worsening of COPD symptoms (COPD exacerbations). A COPD exacerbation is defined as an increase or new onset of more than one COPD symptom such as cough, mucus, shortness of breath, and wheezing that requires medicine beyond your rescue medicine.

SPIRIVA HandiHaler is not a rescue medicine and should not be used for treating sudden breathing problems. Your doctor may give you other medicine to use for sudden breathing problems.

SPIRIVA HandiHaler has not been studied in children.

Who should not take SPIRIVA HandiHaler?

Do not use SPIRIVA HandiHaler if you:

- are allergic to tiotropium. See the end of this leaflet for a complete list of ingredients.
- have had an allergic reaction to ipratropium (Atrovent®).

Allergic reactions may include itching, rash, or swelling of the lips, tongue, or throat (trouble swallowing).

What should I tell my doctor before using SPIRIVA HandiHaler?

Before taking SPIRIVA HandiHaler, tell your doctor about all your medical conditions, including if you:

- have kidney problems.
- have glaucoma. SPIRIVA HandiHaler may make your glaucoma worse.
- have an enlarged prostate, problems passing urine, or a blockage in your bladder. SPIRIVA HandiHaler may make these problems worse.
- are pregnant or plan to become pregnant. It is not known if SPIRIVA HandiHaler could harm your unborn baby.
- are breast-feeding or plan to breast-feed. It is not known if SPIRIVA HandiHaler passes into breast milk. You and your doctor will decide if SPIRIVA HandiHaler is right for you while you breast-feed.
- have a severe allergy to milk proteins. Ask your doctor if you are not sure.

Tell your doctor about all the medicines you take, including prescription and non-prescription medicines and eye drops, vitamins, and herbal supplements. Some of your other medicines or supplements may affect the way SPIRIVA HandiHaler works. SPIRIVA HandiHaler is an anticholinergic medicine. You should not take other anticholinergic medicines while using SPIRIVA HandiHaler, including ipratropium. Ask your doctor or pharmacist if you are not sure if one of your medicines is an anticholinergic.

Know the medicines you take. Keep a list of your medicines with you to show your doctor and pharmacist when you get a new medicine.

How should I take SPIRIVA HandiHaler?

- Use SPIRIVA HandiHaler exactly as prescribed. Use SPIRIVA HandiHaler one time every day.
- Read the “Patient’s Instructions for Use” at the end of this leaflet before you use SPIRIVA HandiHaler. Talk with your doctor if you do not understand the instructions.
- Do not swallow SPIRIVA capsules.
- Only use SPIRIVA capsules with the HandiHaler device.
- Do not use the HandiHaler device to take any other medicine
- SPIRIVA HandiHaler comes as a powder in a SPIRIVA capsule that fits the HandiHaler device. Each SPIRIVA capsule, containing only a small amount of SPIRIVA powder, is one full dose of medicine.
- Separate one blister from the blister card. Then take out one of the SPIRIVA capsules from the blister package right before you use it.
- After the capsule is pierced, take a complete dose of SPIRIVA HandiHaler by breathing in the powder by mouth two times, using the HandiHaler device (take 2 inhalations from one SPIRIVA capsule). See the “Patient’s Instructions for Use” at the end of this leaflet.
- Throw away any SPIRIVA capsule that is not used right away after it is taken out of the blister package. Do not leave the SPIRIVA capsules open to air; they may not work as well.
- If you miss a dose, take it as soon as you remember. Do not use SPIRIVA HandiHaler more than one time every 24 hours.
- If you use more than your prescribed dose of SPIRIVA HandiHaler, call your doctor or a poison control center.

What should I avoid while using SPIRIVA HandiHaler?

Do not let the powder from the SPIRIVA capsule get into your eyes. Your vision may get blurry and the pupil in your eye may get larger (dilate). If this happens, call your doctor.

What are the possible side effects of SPIRIVA HandiHaler?

SPIRIVA HandiHaler can cause serious side effects. If you get any of the following side effects, stop taking SPIRIVA HandiHaler and get medical help right away.

- Allergic reaction. Symptoms may include: itching, rash, swelling of the lips, tongue, or throat (trouble swallowing).
- Sudden narrowing and blockage of the airways into the lungs (bronchospasm). Your breathing suddenly gets worse.
- New or worsened increased pressure in the eyes (acute narrow-angle glaucoma). Symptoms of acute narrow-angle glaucoma may include: eye pain, blurred vision, seeing halos (visual halos) or colored images along with red eyes.
- New or worsened urinary retention. Symptoms of blockage in your bladder and/or enlarged prostate may include: difficulty passing urine, painful urination.

Other side effects with SPIRIVA HandiHaler include:

- upper respiratory tract infection
- dry mouth
- sinus infection
- sore throat
- non-specific chest pain
- urinary tract infection
- indigestion
- runny nose
- constipation
- increased heart rate
- blurred vision

These are not all the possible side effects with SPIRIVA HandiHaler. Tell your doctor if you have any side effect that bothers you or that does not go away.

Call your doctor for medical advice about side effects. You may report side effects to FDA at 1-800-FDA-1088.

How do I store SPIRIVA HandiHaler?

- Do not store SPIRIVA capsules in the HandiHaler device.
- Store SPIRIVA capsules in the sealed blister package at room temperature between 68°F–77°F (20°–25°C).
- Keep SPIRIVA capsules away from heat and cold (do not freeze).
- Store SPIRIVA capsules in a dry place. Throw away any unused SPIRIVA capsules that have been open to air.

Ask your doctor or pharmacist if you have any questions about storing your SPIRIVA capsules.

Keep SPIRIVA HandiHaler, SPIRIVA capsules, and all medicines out of the reach of children.

General information about SPIRIVA HandiHaler
Medicines are sometimes prescribed for purposes other than those listed in Patient Information leaflets. Do not use SPIRIVA HandiHaler for a purpose for which it has not been prescribed. Do not give SPIRIVA HandiHaler to other people even if they have the same symptoms that you have. It may harm them.

For more information about SPIRIVA HandiHaler, talk with your doctor. You can ask your doctor or pharmacist for information about SPIRIVA HandiHaler that is written for health professionals.

For more information about SPIRIVA HandiHaler, you may call Boehringer Ingelheim Pharmaceuticals, Inc. at 1-800-542-6257 or (TTY) 1-800-459-9906.

What are the ingredients in SPIRIVA HandiHaler?

Active ingredient: tiotropium
Inactive ingredient: lactose monohydrate

What is COPD (Chronic Obstructive Pulmonary Disease)?

COPD is a serious lung disease that includes chronic bronchitis, emphysema, or both. Most COPD is caused by smoking. When you have COPD, your airways become narrow. So, air moves out of your lungs more slowly. This makes it hard to breathe.

Distributed by:
Boehringer Ingelheim Pharmaceuticals, Inc.
Ridgefield, CT 06877 USA

Marketed by:
Boehringer Ingelheim Pharmaceuticals, Inc.
Ridgefield, CT 06877 USA
and
Pfizer Inc
New York, NY 10017 USA

Licensed from:
Boehringer Ingelheim International GmbH

SPIRIVA® and HandiHaler® are registered trademarks and are used under license from Boehringer Ingelheim International GmbH.

©Copyright 2009 Boehringer Ingelheim International GmbH
ALL RIGHTS RESERVED

Rev: December 2009

IT1600WL1609
10004551/07
65626-08

Patient's Instructions for Use

SPIRIVA HandiHaler®
(tiotropium bromide inhalation powder)

Important Information: Do not swallow SPIRIVA capsules. SPIRIVA capsules should only be used with the HandiHaler device. SPIRIVA HandiHaler should only be inhaled through your mouth (oral inhalation).

First read the Patient Information that comes with SPIRIVA HandiHaler for important information about using SPIRIVA HandiHaler.

Read these Patient's Instructions for Use before you start to use SPIRIVA HandiHaler and each time you refill your prescription. There may be new information.

For more information, ask your doctor or pharmacist.

SPIRIVA HandiHaler comes with SPIRIVA capsules and a HandiHaler device. The HandiHaler device is an inhalation device that is for use only with SPIRIVA capsules. Do not use the HandiHaler device to take any other medicine.

Becoming familiar with SPIRIVA HandiHaler:

Remove the HandiHaler device from the pouch and become familiar with its components. (Figure A)

1. dust cap
2. mouthpiece
3. mouthpiece ridge
4. base
5. green piercing button
6. center chamber
7. air intake vents

Each SPIRIVA capsule is packaged in a blister. Each blister can be separated from the blister card by tearing along the perforation. (Figure B)

Do not open the SPIRIVA capsule before you insert it into the HandiHaler device. If you open the SPIRIVA capsule, it may not work. Each SPIRIVA capsule contains only a small amount of powder. (Figure C) This is one full dose. The product was designed this way.

How do I inhale the contents of the SPIRIVA capsule using the HandiHaler device?

Taking your dose of medicine using the HandiHaler device has four main steps:

1. Open the HandiHaler device and the blister
2. Insert the SPIRIVA capsule
3. Press the green piercing button
4. Breathe in (inhale) your medicine

(See below for details)

Opening the HandiHaler device:

1. Open the dust cap by pressing the green piercing button. (Figure 1)

Pull the dust cap upwards to expose the mouthpiece. (Figure 2)

Open the mouthpiece by pulling the mouthpiece ridge upwards away from the base. (Figure 3)

Removing a SPIRIVA capsule:

Before removing a SPIRIVA capsule from the blister, separate one of the blisters from the blister card by tearing along the perforation. (Figure 4)

Do not swallow SPIRIVA capsules.

Always store SPIRIVA capsules in the sealed blisters. Remove only one SPIRIVA capsule from the blister right before use. Do not store SPIRIVA capsules in the HandiHaler device. Inhale the contents of the SPIRIVA capsule using the HandiHaler device right away after the blister packaging of an individual SPIRIVA capsule is opened, or else it may not work as well.

Right before you are ready to use your SPIRIVA HandiHaler:

Bend back and forth one of the corners of the blister that has an arrow and then with your finger separate the aluminum foil layers. Carefully peel back the printed foil until you can see the whole SPIRIVA capsule. (Figure 5)

Turn the blister upside down and tip the SPIRIVA capsule out, tapping the back of the blister, if needed.

Do not cut the foil or use sharp instruments to take out the SPIRIVA capsule from the blister.

If more SPIRIVA capsules are opened to air, they should not be used and should be thrown away.

Inserting the SPIRIVA capsule into the HandiHaler device:

2. Insert (put) the SPIRIVA capsule in the center chamber of the HandiHaler device. It does not matter which end of the SPIRIVA capsule you put in the chamber. (Figure 6)

Close the mouthpiece until you hear a click, but leave the dust cap open. (Figure 7)
Be sure that you have the mouthpiece sitting firmly against the gray base.

Taking your dose using the HandiHaler device:

`

Hold the HandiHaler device with the mouthpiece upright. It is important that you hold the HandiHaler device in an upright position (Figure 8) when pressing the green piercing button.

3. Press the green piercing button until it is flat (flush) against the base, and release. This is how you make holes in the SPIRIVA capsule so that you get the medicine when you breathe in.

Do not press the green button more than one time.

Breathe out completely. (Figure 9)

Important: Do not breathe (exhale) into the mouthpiece of the HandiHaler device at any time.

4. Breathe in (inhale)

- Hold the HandiHaler device by the gray base. Do not block the air intake vents.
- Raise the HandiHaler device to your mouth and close your lips tightly around the mouthpiece.
- Keep your head in an upright position. The HandiHaler device should be in a horizontal position. (Figure 10)
- Breathe in slowly and deeply so that you hear or feel the SPIRIVA capsule vibrate.
- Breathe in until your lungs are full.
- Hold your breath as long as is comfortable and at the same time take the HandiHaler device out of your mouth. Breathe normally again.

To make sure you get the full dose, you must breathe out completely, and inhale again as in step 4 above (Figure 10). Do not press the green piercing button again.

If you do not hear or feel the SPIRIVA capsule vibrate, do not press the green piercing button again. Instead, hold the HandiHaler device in an upright position and tap the HandiHaler device gently on a table. (Figure 11)

Check to see that the mouthpiece is completely closed. Then, breathe in again – slowly and deeply.

If you still do not hear or feel the SPIRIVA capsule vibrate after repeating the above steps, throw away the SPIRIVA capsule. Open the base by lifting the green piercing button and check the center chamber for pieces of the SPIRIVA capsule (SPIRIVA capsule fragments). SPIRIVA capsule fragments in the center chamber can cause a SPIRIVA capsule not to vibrate. Turn the HandiHaler device upside down and gently tap to remove the SPIRIVA capsule fragments. Call your doctor for instructions.

After you finish taking your daily dose of SPIRIVA HandiHaler, open the mouthpiece again. Tip out the used SPIRIVA capsule and throw it away. (Figure 12)

Close the mouthpiece and dust cap for storage of your HandiHaler device. (Figure 13)

Do not store used or unused SPIRIVA capsules in the HandiHaler device.

When and how should I clean my HandiHaler device?

Clean the HandiHaler device one time each month or as needed. (Figure 14)

- Open the dust cap and mouthpiece.
- Open the base by lifting the green piercing button.
- Look at the center chamber for SPIRIVA capsule fragments or powder residue.
- Rinse the HandiHaler device with warm water. Check that any powder buildup or SPIRIVA capsule fragments are removed.
- Do not use cleaning agents or detergents.
- Do not place the HandiHaler device in the dishwasher for cleaning.
- Dry the HandiHaler device well by tipping the excess water out on a paper towel. Air-dry afterwards, leaving the dust cap, mouthpiece, and base open.
- Do not use a hair dryer to dry the HandiHaler device.
- It takes 24 hours to air dry, so clean the HandiHaler device right after you use it so that it will be ready for your next dose.
- Do not use the HandiHaler device when it is wet. If needed, you may clean the outside of the mouthpiece with a clean damp cloth.

Distributed by:
Boehringer Ingelheim Pharmaceuticals, Inc.
Ridgefield, CT 06877 USA

Marketed by:
Boehringer Ingelheim Pharmaceuticals, Inc.
Ridgefield, CT 06877 USA
and
Pfizer Inc
New York, NY 10017 USA

Licensed from:
Boehringer Ingelheim International GmbH

SPIRIVA® and HandiHaler® are registered trademarks and are used under license from Boehringer Ingelheim International GmbH

©Copyright 2009 Boehringer Ingelheim International GmbH
ALL RIGHTS RESERVED

Rev: December 2009

IT1600WL1609
10004551/07
65626-08

PACKAGE LABEL

SPIRIVA HandiHaler

30 capsules (5 blister cards)

1 HandiHaler Inhalation Device